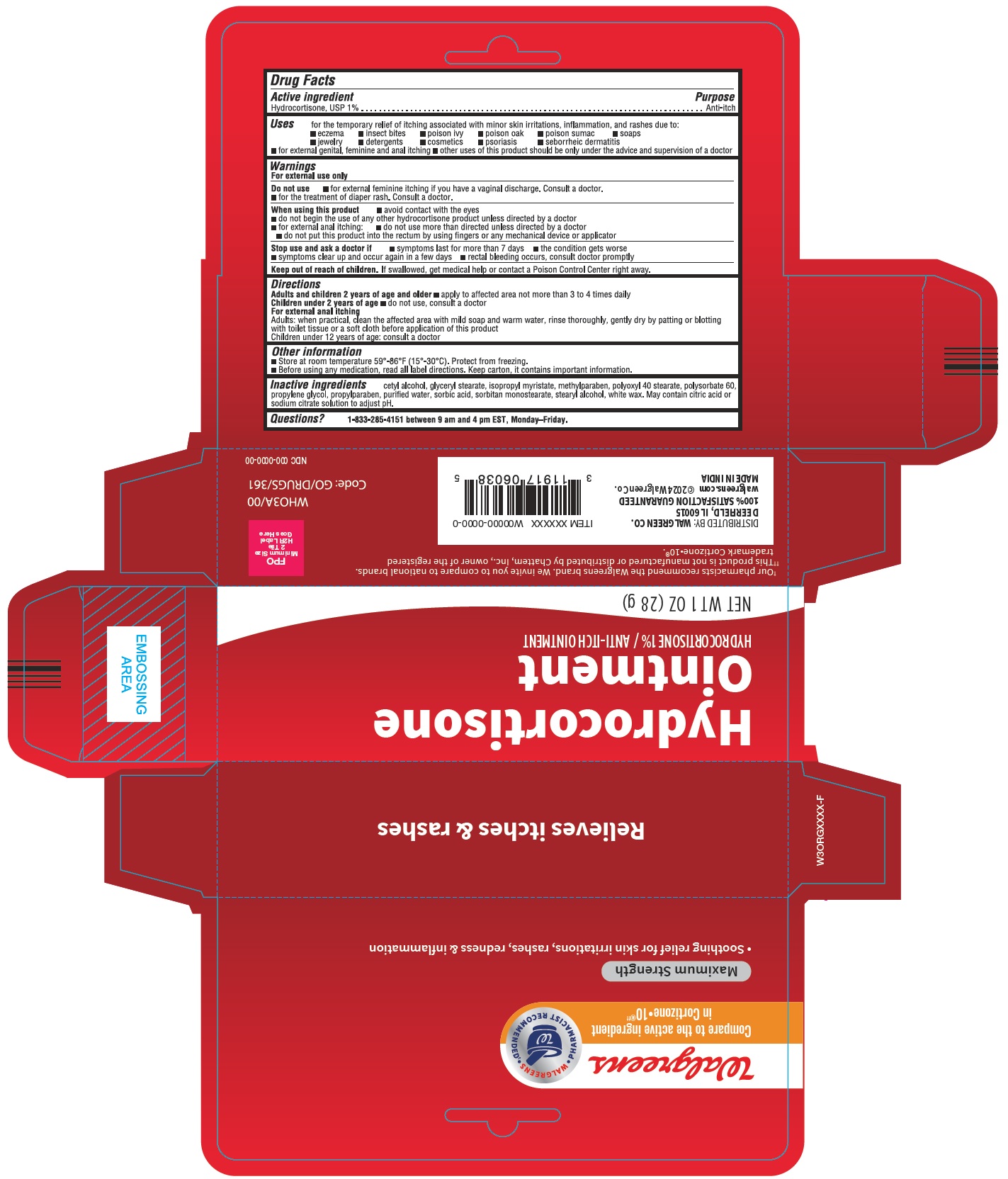 DRUG LABEL: Hydrocortisone
NDC: 0363-1333 | Form: OINTMENT
Manufacturer: Walgreens Co.
Category: otc | Type: Human OTC Drug Label
Date: 20250306

ACTIVE INGREDIENTS: HYDROCORTISONE 1 g/100 g
INACTIVE INGREDIENTS: CETYL ALCOHOL; GLYCERYL STEARATE; ISOPROPYL MYRISTATE; METHYLPARABEN; POLYOXYL 40 STEARATE; POLYSORBATE 40; PROPYLENE GLYCOL; PROPYLPARABEN; WATER; SORBIC ACID; SORBITAN MONOSTEARATE; STEARYL ALCOHOL; WHITE WAX; SODIUM CITRATE

Hydrocortisone Ointment 1%

ACTIVE INGREDIENT(S)

Hydrocortisone, USP 1%

PURPOSE

Anti-itch

USE(S)

for the temporary relief of itching associated with minor skin irritations, inflammation, and rashes due to:

- eczema
- insect bites
- poison ivy
- poison oak
- poison sumac
- soaps
- jewelry
- detergents
- cosmetics
- psoriasis
- seborrheic dermatitis
- for external genital, feminine and anal itching
- other uses of this product should be only under the advice and supervision of a doctor

WARNINGS

For external use only

DO NOT USE

- for external feminine itching if you have a vaginal discharge. Consult a doctor.
- for the treatment of diaper rash. Consult a doctor.

WHEN USING THIS PRODUCT

- avoid contact with the eyes
- do not begin the use of any other hydrocortisone product unless directed by a doctor
- for external anal itching:
- do not use more than directed unless directed by a doctor
- do not put this product into the rectum by using fingers or any mechanical device or applicator

STOP USE AND ASK A DOCTOR IF

- symptoms last for more than 7 days
- the condition gets worse, symptoms clear up and occur again in a few days
- rectal bleeding occurs, consult doctor promptly

KEEP OUT OF REACH OF CHILDREN

If swallowed, get medical help or contact a Poison Control Center right away.

DIRECTIONS

Adults and children 2 years of age and older apply to affected area not more than 3 to 4 times daily.

Children under 2 years of age do not use, consult a doctor.

For external anal itching

Adults: when practical, clean the affected area with mild soap and warm water, rinse thoroughly, gently dry by patting or blotting with toilet tissue or a soft cloth before application of this product.

Children under 12 years of age: consult a doctor

OTHER INFORMATION

- Store at room temperature 59^0-86^0F (15^0-30^0C). Protect from freezing.
- Before using any medication, read all label directions. Keep carton, it contains important information.

INACTIVE INGREDIENT

cetyl alcohol, glyceryl stearate, isopropyl myristate, methylparaben, polyoxyl 40 stearate, polysorbate 60, propylene glycol, propylparaben, purified water, sorbic acid, sorbitan monostearate, stearyl alcohol, white wax, May contain citric acid or sodium citrate solution to adjust pH.

QUESTIONS?

1-833-285-4151 between 9 am and 4 pm EST, Monday-Friday.